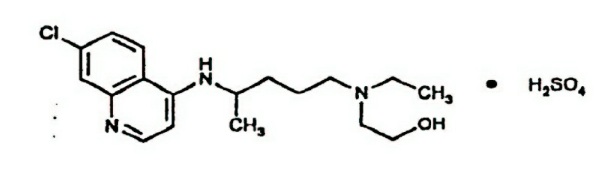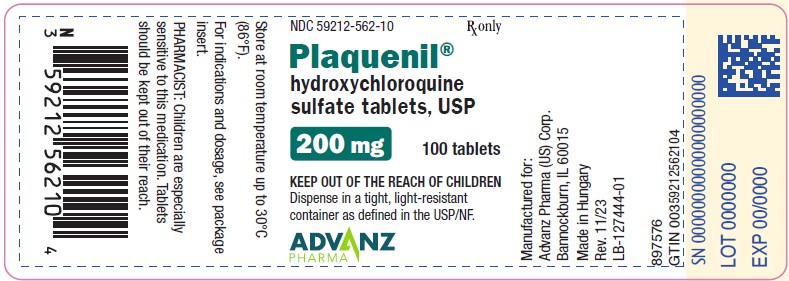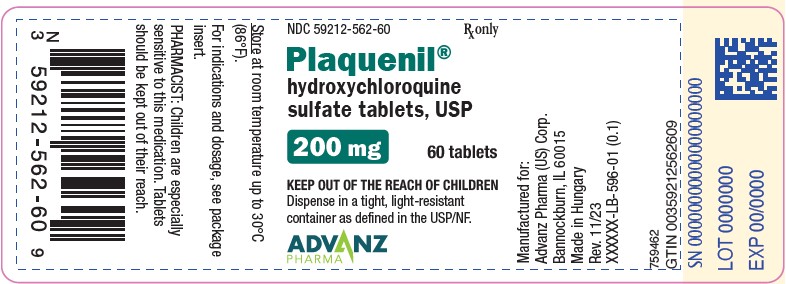 DRUG LABEL: Plaquenil
NDC: 59212-562 | Form: TABLET
Manufacturer: Advanz Pharma (US) Corp.
Category: prescription | Type: Human Prescription Drug Label
Date: 20241205

ACTIVE INGREDIENTS: hydroxychloroquine sulfate 200 mg/1 1
INACTIVE INGREDIENTS: Calcium Phosphate, Dibasic, Anhydrous; HYPROMELLOSE 2910 (6 MPA.S); Magnesium Stearate; Polyethylene glycol 400; Polysorbate 80; Starch, Corn; Titanium Dioxide; CARNAUBA WAX; FERROSOFERRIC OXIDE

HIGHLIGHTS OF PRESCRIBING INFORMATION

These highlights do not include all the information needed to use PLAQUENIL® safely and effectively. See full prescribing information for PLAQUENIL.
PLAQUENIL (hydroxychloroquine sulfate) tablets, for oral use
Initial U.S. Approval: 1955

RECENT MAJOR CHANGES

Warnings and Precautions, Risks Associated with Use in Porphyria (5.5) ... 7/2023

Warnings and Precautions, Neuropsychiatric Reactions Including Suicidality (5.9) ... 7/2023

1 INDICATIONS AND USAGE

PLAQUENIL is an antimalarial and antirheumatic indicated for the:
• Treatment of uncomplicated malaria due to Plasmodium falciparum, Plasmodium malariae, Plasmodium ovale, and Plasmodium vivax in adult and pediatric patients. (1.1)
• Prophylaxis of malaria in geographic areas where chloroquine resistance is not reported in adult and pediatric patients. (1.1)
• Treatment of rheumatoid arthritis in adults.(1.2)
• Treatment of systemic lupus erythematosus in adults.(1.3)
• Treatment of chronic discoid lupus erythematosus in adults. (1.4)
Limitations of Use (1.1):
PLAQUENIL is not recommended for the:
• Treatment of complicated malaria.
• Treatment of chloroquine or hydroxychloroquine-resistant strains of Plasmodium species.
• Treatment of malaria acquired in geographic areas where chloroquine resistance occurs or when the Plasmodium species has not been identified.
• Prophylaxis of malaria in geographic areas where chloroquine resistance occurs.
• Prevention of relapses of P. vivax or P. ovale because it is not active against the hypnozoite liver stage forms of these parasites. For radical cure of P. vivax and P. ovale infections, concomitant therapy with an 8-aminoquinoline drug is necessary.

2 DOSAGE AND ADMINISTRATION

Malaria in Adult and Pediatric Patients (2.2):

- Prophylaxis: Begin weekly doses 2 weeks prior to travel to the endemic area, continue weekly doses while in the endemic area, and continue the weekly doses for 4 weeks after leaving the endemic area:
  - Adults: 400 mg once a week
  - Pediatric patients ≥ 31 kg: 6.5 mg/kg up to 400 mg, once a week
- Treatment of Uncomplicated Malaria: See Full Prescribing Information (FPI) for complete dosing information.

Rheumatoid Arthritis in Adults (2.3):

- Initial dosage: 400 mg to 600 mg daily
- Chronic dosage: 200 mg once daily or 400 mg once daily (or in two divided doses)

Systemic Lupus Erythematosus in Adults (2.4):

- 200 mg once daily or 400 mg once daily (or in two divided doses)

Chronic Discoid Lupus Erythematosus in Adults (2.5):

- 200 mg once daily or 400 mg once daily (or in two divided doses)

3 DOSAGE FORMS AND STRENGTHS

Tablets: 200 mg of hydroxychloroquine sulfate

4 CONTRAINDICATIONS

• Patients with hypersensitivity to 4-aminoquinoline compounds (4)

5 WARNINGS AND PRECAUTIONS

• Cardiomyopathy and Ventricular Arrhythmias: Fatal or life-threatening cardiomyopathy and ventricular arrhythmias were reported. (5.1)
• Retinal Toxicity: Irreversible retinal damage is related to cumulative dosage and treatment duration. Baseline retinal exam and exams during treatment are recommended.(5.2)
• Serious Skin Reactions: Stevens Johnson syndrome, toxic epidermal necrolysis, drug reaction with eosinophilia and systemic symptoms, acute generalized exanthematous pustulosis have been reported. (5.3)
• Worsening of Psoriasis: Avoid in patients with psoriasis. (5.4)

• Risks Associated with Use in Porphyria: Avoid in patients with porphyria. Hepatotoxicity was reported in patients with porphyria cutanea tarda. (5.5)

• Hematologic Toxicity: Discontinue if myelosuppression occurs. (5.6)

•Renal Toxicity: Consider phospholipidosis as a possible cause of renal injury in patients with underlying connective tissue disorders. Discontinue PLAQUENIL if renal toxicity is suspected or demonstrated by tissue biopsy in any organ system. (5.1, 5.8, 5.11)

6 ADVERSE REACTIONS

The most common adverse reactions reported are: nausea, vomiting, diarrhea, and abdominal pain. (6)
To report SUSPECTED ADVERSE REACTIONS, contact Advanz Pharma (US) Corp. at 1-877-370-1142 or FDA at 1-800-FDA-1088 or www.fda.gov/medwatch.

7 DRUG INTERACTIONS

• Drugs Prolonging QT Interval and Other Arrhythmogenic Drugs. (7.1)
• See FPI for more important drug interactions.(7)

FULL PRESCRIBING INFORMATION

1 INDICATIONS AND USAGE

1.1 Malaria

PLAQUENIL is indicated in adult and pediatric patients for the:
• Treatment of uncomplicated malaria due to Plasmodium falciparum, Plasmodium malariae, Plasmodium vivax, and Plasmodium ovale.
• Prophylaxis of malaria in geographic areas where chloroquine resistance is not reported.
Limitations of Use:
PLAQUENIL is not recommended for:
• Treatment of complicated malaria.
• Treatment of malaria by chloroquine or hydroxychloroquine-resistant strains of Plasmodium species [see Microbiology (12.4)].
• Treatment of malaria acquired in geographic areas where chloroquine resistance occurs or when the Plasmodium species has not been identified.
• Prophylaxis of malaria in geographic areas where chloroquine resistance occurs.
• Prevention of relapses of P. vivax or P. ovale because it is not active against the hypnozoite liver stage forms of these parasites. For radical cure of P. vivax and P. ovale infections, concomitant therapy with an 8-aminoquinoline drug is necessary [see Microbiology (12.4)].
For the most current information about drug resistance, refer to the latest recommendations from the Center for Disease Control and Prevention1
.

1.2 Rheumatoid Arthritis

PLAQUENIL is indicated for the treatment of acute and chronic rheumatoid arthritis in adults.

1.3 Systemic Lupus Erythematosus

PLAQUENIL is indicated for the treatment of systemic lupus erythematosus in adults.

1.4 Chronic Discoid Lupus Erythematosus

PLAQUENIL is indicated for the treatment of chronic discoid lupus erythematosus in adults.

2 DOSAGE AND ADMINISTRATION

2.1 Important Administration Instructions

Administer PLAQUENIL orally with food or milk. Do not crush or divide the tablets.

2.2 Dosage for Malaria in Adult and Pediatric Patients

PLAQUENIL is not recommended in pediatric patients less than 31 kg because the lowest available strength (200 mg) exceeds the recommended dose for these patients and it cannot be divided.
Prophylaxis
Treatment must start 2 weeks before travel to an endemic area. Advise the patient to take the prophylaxis dosage once a week, staring 2 weeks prior to travel to the endemic area, on the same day every week, continuing the same weekly dose while in the endemic area, and for 4 weeks after leaving the endemic area. The recommended prophylaxis dosage is:
• Adult patients: 400 mg once a week
• Pediatric patients ≥ 31kg: 6.5 mg/kg actual body weight (up to 400 mg) once a week
Treatment of Uncomplicated Malaria
The dosages for the treatment of uncomplicated malaria are:
• Adult patients: Administer 800 mg initially; subsequently administer 400 mg at 6 hours, 24 hours, and 48 hours after the initial dose (total dosage = 2000 mg).
• Pediatric patients ≥ 31 kg: Administer 13 mg/kg (up to 800 mg) initially; subsequently administer 6.5 mg/kg (up to 400 mg) at 6 hours, 24 hours, and 48 hours after the initial dose (total dosage = 31 mg/kg - up to 2000 mg).
For radical cure of P. vivax and P. ovale infections, concomitant therapy with an 8-aminoquinoline drug is necessary [see Microbiology (12.4)].

2.3 Dosage for Rheumatoid Arthritis in Adults

The recommended dosage is:
• Initial dosage: 400 mg to 600 mg daily as a single daily dose or two divided doses. The action of hydroxychloroquine is cumulative and may require weeks to months for maximum therapeutic effect. Daily doses exceeding 5 mg/kg (actual weight) of hydroxychloroquine sulfate increase the incidence of retinopathy [see Warnings and Precautions (5.2)].
• Chronic dosage: 200 mg once daily to 400 mg daily, as a single dose or two divided doses.
Corticosteroids, salicylates, and other antirheumatic agents may be used concomitantly with PLAQUENIL.

2.4 Dosage for Systemic Lupus Erythematosus in Adults

The recommended dosage is 200 mg given once daily, or 400 mg given once daily or in two divided doses.

2.5 Dosage for Chronic Discoid Lupus Erythematosus in Adults

The recommended dosage is 200 mg given once daily, or 400 mg given once daily or in two divided doses.

3 DOSAGE FORMS AND STRENGTHS

Tablets: 200 mg of hydroxychloroquine sulfate, white to off-white, film-coated tablet imprinted with “PLAQUENIL” on one face in black ink.

4 CONTRAINDICATIONS

PLAQUENIL is contraindicated in patients with known hypersensitivity to 4-aminoquinoline compounds.

5 WARNINGS AND PRECAUTIONS

5.1 Cardiomyopathy and Ventricular Arrhythmias

Fatal and life-threatening cases of cardiotoxicity, including cardiomyopathy, have been reported in patients treated with PLAQUENIL. Signs and symptoms of cardiac compromise have occurred during acute and chronic PLAQUENIL treatment. In multiple cases, endomyocardial biopsy showed association of the cardiomyopathy with phospholipidosis in the absence of inflammation, infiltration, or necrosis. Drug-induced phospholipidosis may occur in other organ systems [see Warnings and Precautions (5.8, 5.11)].

Patients may present with ventricular hypertrophy, pulmonary hypertension and conduction disorders including sick sinus syndrome. ECG findings include atrioventricular, right or left bundle branch block.

PLAQUENIL has a potential to prolong the QT interval. Ventricular arrhythmias (including torsades de pointes) have been reported in PLAQUENIL-treated patients. The magnitude of QT prolongation may increase with increasing concentrations of the drug. Therefore, the recommended dose should not be exceeded [see Adverse Reactions (6), Overdosage (10)]. Avoid PLAQUENIL administration in patients with congenital or documented acquired QT prolongation and/or known risk factors for prolongation of the QT interval such as:
• Cardiac disease, e.g., heart failure, myocardial infarction.
• Proarrhythmic conditions, e.g., bradycardia (< 50 bpm).
• History of ventricular dysrhythmias.
• Uncorrected hypokalemia and/or hypomagnesemia.
• Concomitant administration with QT interval prolonging agents as this may lead to an increased risk for ventricular arrhythmias [see Drug Interactions (7.1)].
Therefore, PLAQUENIL is not recommended in patients taking other drugs that have the potential to prolong the QT interval. Correct electrolyte imbalances prior to use. Monitor cardiac function as clinically indicated during PLAQUENIL therapy. Discontinue PLAQUENIL if cardiotoxicity is suspected or demonstrated by tissue biopsy.

5.2 Retinal Toxicity

Irreversible retinal damage was observed in some patients treated with hydroxychloroquine sulfate and it is related to cumulative dosage and treatment duration. In patients of Asian descent, retinal toxicity may first be noticed outside the macula.
Risk factors for retinal damage include daily hydroxychloroquine sulfate dosages ≥5 mg/kg of actual body weight, durations of use greater than five years, renal impairment, use of concomitant drug products such as tamoxifen citrate, and concurrent macular disease.
Within the first year of starting PLAQUENIL, a baseline ocular examination is recommended including best corrected distance visual acuity (BCVA), an automated threshold visual field (VF) of the central 10 degrees (with retesting if an abnormality is noted), and spectral domain ocular coherence tomography (SD-OCT). For patients at higher risk of retinal damage, monitoring should include annual examinations which include BCVA, VF and SD-OCT. For patients without significant risk factors, annual retinal exams can usually be deferred until five years of treatment. In patients of Asian descent, it is recommended that visual field testing be performed in the central 24 degrees instead of the central 10 degrees.
If ocular toxicity is suspected, discontinue PLAQUENIL and monitor the patient closely given that retinal changes and visual disturbances may progress even after cessation of therapy.

5.3 Serious Skin Reactions

Serious adverse reactions have been reported with the use of PLAQUENIL including Stevens-Johnson syndrome (SJS), toxic epidermal necrolysis (TEN), drug reaction with eosinophilia and systemic symptoms (DRESS syndrome), acute generalized exanthematous pustulosis (AGEP). Monitor for serious skin reactions, especially in patients receiving a drug that may also induce dermatitis. Advise patients to seek medical attention promptly if they experience signs and symptoms of serious skin reactions such as blisters on the skin, eyes, lips or in the mouth, itching or burning, with or without fever [see Warnings and Precautions (5.4, 5.5), Adverse Reactions (6)]. Discontinue PLAQUENIL if these severe reactions occur.

5.4 Worsening of Psoriasis

Administration of PLAQUENIL to patients with psoriasis may precipitate a severe flare-up of psoriasis. Avoid PLAQUENIL in patients with psoriasis, unless the benefit to the patient outweighs the possible risk.

5.5 Risks Associated with Use in Porphyria

Administration of PLAQUENIL to patients with porphyria may exacerbate porphyria. Avoid PLAQUENIL in patients with porphyria.

Hepatotoxicity Associated with Porphyria Cutanea Tarda

Cases of hepatotoxicity have been reported when hydroxychloroquine was used in patients with porphyria cutanea tarda (PCT). Patients received dosages ranging from 200 mg twice weekly to 400 mg daily. Most of the PCT-related cases presented with marked elevations in transaminases (>20 times upper limit of the reference range) within days to a month of hydroxychloroquine initiation. In some cases, PCT was diagnosed only after the occurrence of treatment-induced liver injury, when hydroxychloroquine was prescribed for an approved indication. Some of the cases were associated with other risk factors for hepatic injury (e.g., alcohol use, concomitant hepatotoxic medications).

Measure liver tests promptly in patients who report symptoms that may indicate liver injury, such as fatigue, rash, nausea, dark urine, or jaundice. In this clinical context, if the patient is found to have abnormal serum liver tests (e.g., ALT level greater than three times the upper limit of the reference range, total bilirubin greater than two times the upper limit of the reference range), interrupt treatment with PLAQUENIL, and investigate further to establish the probable cause.

The safety and effectiveness of PLAQUENIL for the treatment of PCT have not been established and PLAQUENIL is not approved for this use.

5.6 Hematologic Toxicity

PLAQUENIL may cause myelosuppression including aplastic anemia, agranulocytosis, leukopenia, or thrombocytopenia. Monitor blood cell counts periodically in patients on prolonged PLAQUENIL therapy. If the patient develops myelosuppression which cannot be attributable to the disease, discontinue the drug.

5.7 Hemolytic Anemia Associated with G6PD Deficiency

Hemolysis has been reported in patients with glucose-6-phosphate dehydrogenase (G6PD) deficiency. Monitor for hemolytic anemia as this can occur, particularly in association with other drugs that cause hemolysis.

5.8 Skeletal Muscle Myopathy or Neuropathy

Skeletal muscle myopathy or neuropathy leading to progressive weakness and atrophy of proximal muscle groups, depressed tendon reflexes, and abnormal nerve conduction, have been reported. Muscle and nerve biopsies have shown associated phospholipidosis. Drug-induced phospholipidosis may occur in other organ systems [see Warnings and Precautions (5.1, 5.11)].
Assess muscle strength and deep tendon reflexes periodically in patients on long-term therapy with PLAQUENIL. Discontinue PLAQUENIL if muscle or nerve toxicity is suspected or demonstrated by tissue biopsy.

5.9 Neuropsychiatric Reactions Including Suicidality

Suicidal behavior, suicidal ideation, and other neuropsychiatric adverse reactions have been reported in patients treated with PLAQUENIL [see Adverse Reactions (6)]. Neuropsychiatric adverse reactions typically occurred within the first month after the start of treatment with hydroxychloroquine and have been reported in patients with and without a prior history of psychiatric disorders.

The risks and benefits of continued treatment with PLAQUENIL should be assessed for patients who develop these symptoms. Given the long half-life of the drug, some patients may require several weeks off drug for symptoms to partially or fully abate.

Advise patients to contact their healthcare provider promptly if they experience new or worsening neuropsychiatric symptoms such as depression, suicidal thoughts or behavior, or mood changes.

5.10 Hypoglycemia

PLAQUENIL can cause severe and potentially life-threatening hypoglycemia, in the presence or absence of antidiabetic agents [see Drug Interactions (7)]. Measure blood glucose in patients presenting with clinical symptoms suggestive of hypoglycemia and as adjust the antidiabetic treatment as necessary. Warn PLAQUENIL-treated patients about the risk of hypoglycemia and educate them on the signs and symptoms of hypoglycemia; diabetic patients should monitor their blood sugar levels. Advise patients to seek medical attention if they develop any signs and symptoms of hypoglycemia.

5.11 Renal Toxicity

Proteinuria with or without moderate reduction in glomerular filtration rate have been reported with the use of PLAQUENIL.
Renal biopsy showed phospholipidosis without immune deposits, inflammation, and/or increased cellularity. Physicians should consider phospholipidosis as a possible cause of renal injury in patients with underlying connective tissue disorders who are receiving PLAQUENIL. Drug-induced phospholipidosis may occur in other organ systems [see Warnings and Precautions (5.1, 5.8)]. Discontinue PLAQUENIL if renal toxicity is suspected or demonstrated by tissue biopsy.

6 ADVERSE REACTIONS

The following adverse reactions are described in greater detail in other sections:
• Cardiomyopathy and Ventricular Arrhythmias [see Warnings and Precautions (5.1)]
• Retinal Toxicity [see Warnings and Precautions (5.2)]
• Serious Skin Reactions [see Warnings and Precautions (5.3)]
• Worsening of Psoriasis [see Warnings and Precautions (5.4)]
• Risks Associated with Use in Porphyria [see Warnings and Precautions (5.5)]
• Hematologic Toxicity [see Warnings and Precautions (5.6)]
• Hemolytic Anemia Associated with G6PD [see Warnings and Precautions (5.7)]
• Skeletal Muscle Myopathy or Neuropathy [see Warnings and Precautions (5.8)]
• Neuropsychiatric Reactions Including Suicidality [see Warnings and Precautions (5.9)]
• Hypoglycemia [see Warnings and Precautions (5.10)]

• Renal Toxicity [see Warnings and Precautions (5.11)]

The following adverse reactions have been identified during post-approval use of 4-aminoquinoline drugs, including PLAQUENIL. Because these reactions are reported voluntarily from a population of uncertain size, it is not always possible to reliably estimate their frequency or establish a causal relationship to drug exposure:
- Blood and lymphatic system disorders: Bone marrow depression, anemia, aplastic anemia, agranulocytosis, leukopenia, thrombocytopenia
- Cardiac disorders: Cardiomyopathy, cardiac failure, QT-interval prolongation, ventricular tachycardia, torsades de pointes, atrioventricular block, bundle branch block, sick sinus syndrome, pulmonary hypertension
- Ear and labyrinth disorders: Vertigo, tinnitus, nystagmus, sensorineural hearing loss
- Eye disorders: Retinopathy, retinal pigmentation changes (typically bull’s eye appearance), visual field defects (paracentral scotomas), macular degeneration, corneal edema, corneal opacities, decreased dark adaptation
- Gastrointestinal disorders: Nausea, vomiting, diarrhea, abdominal pain
- General disorders: Fatigue
- Hepatobiliary disorders: Abnormal liver function tests, fulminant hepatic failure
- Immune system disorders: Urticaria, angioedema, bronchospasm
- Metabolism and nutrition disorders: Anorexia, hypoglycemia, weight loss
- Musculoskeletal and connective tissue disorders: Proximal myopathy, depressed tendon reflexes, abnormal nerve conduction
- Nervous system disorders: Ataxia, dizziness, headache, seizure, extrapyramidal disorders (dystonia, dyskinesia, tremor)
-Neuropsychiatric disorders: Affect/emotional lability, irritability, nervousness, psychosis, suicidal ideation, suicidal behavior, depression, hallucinations, anxiety, agitation, confusion, delusions, paranoia, mania, and sleep disorders (insomnia, night terrors, nightmares)
- Skin and subcutaneous tissue disorders: Alopecia, hair color changes, rash, pruritus, photosensitivity, psoriasis exacerbation, hyperpigmentation, exfoliative dermatitis, erythema multiforme, acute generalized exanthematous pustulosis, Drug Rash with Eosinophilia and Systemic Symptoms (DRESS syndrome), Stevens-Johnson syndrome (SJS), toxic epidermal necrolysis (TEN)

7 DRUG INTERACTIONS

7.1 Drugs Prolonging QT Interval and Other Arrhythmogenic Drugs

PLAQUENIL prolongs the QT interval. There may be an increased risk of inducing ventricular arrhythmias if PLAQUENIL is used concomitantly with other arrhythmogenic drugs. Therefore, PLAQUENIL is not recommended in patients taking other drugs that have the potential to prolong the QT interval or are arrhythmogenic [see Warnings and Precautions (5.1)].

7.2 Insulin or Other Antidiabetic Drugs

PLAQUENIL may enhance the effects of insulin and antidiabetic drugs, and consequently increase the hypoglycemic risk. Therefore, a decrease in dosage of insulin and other antidiabetic drugs may be necessary [see Warnings and Precautions (5.10)].

7.3 Drugs that Lower the Seizure Threshold

PLAQUENIL can lower the seizure threshold. Co-administration of PLAQUENIL with other antimalarials known to lower the seizure threshold (e.g., mefloquine) may increase the risk of seizures.

7.4 Antiepileptics

The activity of antiepileptic drugs might be impaired if co-administered with PLAQUENIL.

7.5 Methotrexate

Concomitant use of PLAQUENIL and methotrexate may increase the incidence of adverse reactions.

7.6 Cyclosporine

An increased plasma cyclosporin level was reported when cyclosporin and PLAQUENIL were co-administered. Monitor serum cyclosporine levels closely in patients receiving combined therapy.

7.7 Digoxin

Concomitant PLAQUENIL and digoxin therapy may result in increased serum digoxin levels. Monitor serum digoxin levels closely in patients receiving combined therapy.

7.8 Cimetidine

Concomitant use of cimetidine resulted in a 2-fold increase of exposure of chloroquine, which is structurally related to hydroxychloroquine. Interaction of cimetidine with hydroxychloroquine cannot be ruled out. Avoid concomitant use of cimetidine

7.9 Rifampicin

Lack of efficacy of hydroxychloroquine was reported when rifampicin was concomitantly administered. Avoid concomitant use of rifampicin.

7.10 Praziquantel

Chloroquine has been reported to reduce the bioavailability of praziquantel. Interaction of praziquantel with hydroxychloroquine cannot be ruled out.

7.11 Antacids and kaolin

Antacids and kaolin can reduce absorption of chloroquine; an interval of at least 4 hours between intake of these agents and chloroquine should be observed. Interaction of antacids and kaolin with hydroxychloroquine cannot be ruled out.

7.12 Ampicillin

In a study of healthy volunteers, chloroquine significantly reduced the bioavailability of ampicillin. Interaction of ampicillin with hydroxychloroquine cannot be ruled out.

8 USE IN SPECIFIC POPULATIONS

8.1 Pregnancy

Pregnancy Exposure Registry
There is a pregnancy exposure registry that monitors pregnancy outcomes in women exposed to PLAQUENIL during pregnancy. Encourage patients to register by contacting 1-877-311-8972.
Risk Summary
Prolonged clinical experience over decades of use and available data from published epidemiologic and clinical studies with PLAQUENIL use in pregnant women have not identified a drug-associated risk of major birth defects, miscarriage, or adverse maternal, or fetal outcomes (see Data). There are risks to the mother and fetus associated with untreated or increased disease activity from malaria, rheumatoid arthritis, and systemic lupus erythematosus in pregnancy (see Clinical Considerations). Animal reproduction studies were not conducted with hydroxychloroquine.
The estimated background risk of major birth defects and miscarriage for the indicated populations is unknown. All pregnancies have a background risk of birth defect, loss, or other adverse outcomes. In the US general population, the estimated background risk of major birth defects and miscarriage in clinically recognized pregnancies is 2-4% and 15-20%, respectively.
Clinical Considerations
Disease-Associated Maternal and/or Embryo-Fetal Risk
Malaria: Malaria during pregnancy increases the risk for adverse pregnancy outcomes, including maternal anemia, prematurity, spontaneous abortion, and stillbirth.
Rheumatoid Arthritis: Published data suggest that increased disease activity is associated with the risk of developing adverse pregnancy outcomes in women with rheumatoid arthritis Adverse pregnancy outcomes include preterm delivery (before 37 weeks of gestation), low birth weight (less than 2500 g) infants, and small for gestational age at birth.
Systemic Lupus Erythematosus: Pregnant women with systemic lupus erythematosus, especially those with increased disease activity, are at increased risk of adverse pregnancy outcomes, including spontaneous abortion, fetal death, preeclampsia, preterm birth, and intrauterine growth restriction. Passage of maternal auto-antibodies across the placenta may result in neonatal illness, including neonatal lupus and congenital heart block.
Data
Human Data
Data from published epidemiologic and clinical studies have not established an association with PLAQUENIL use during pregnancy and major birth defects, miscarriage, or adverse maternal or fetal outcomes. Hydroxychloroquine readily crosses the placenta with cord blood levels corresponding to maternal plasma levels. No retinal toxicity, ototoxicity, cardiotoxicity, or growth and developmental abnormalities have been observed in children who were exposed to hydroxychloroquine in utero. Available epidemiologic and clinical studies have methodological limitations including small sample size and study design.

8.2 Lactation

Risk Summary
Published lactation data report that hydroxychloroquine is present in human milk at low levels. No adverse reactions have been reported in breastfed infants. No retinal toxicity, ototoxicity, cardiotoxicity, or growth and developmental abnormalities have been observed in children who were exposed to hydroxychloroquine through breastmilk. There is no information on the effect of hydroxychloroquine on milk production. The developmental and health benefits of breastfeeding should be considered along with the mother’s clinical need for PLAQUENIL and any potential adverse effects on the breastfed child from PLAQUENIL or from the underlying maternal condition.

8.4 Pediatric Use

The safety and effectiveness of PLAQUENIL have been established in pediatric patients for the treatment of uncomplicated malaria due to P. falciparum, P. malariae, P. vivax, and P. ovale, as well as for the prophylaxis of malaria in geographic areas where chloroquine resistance is not reported. However, this product cannot be directly administered to pediatric patients weighing less than 31 kg because the film-coated tablets cannot be crushed or divided [see Dosage and Administration (2.1, 2.2)].
The safety and effectiveness of PLAQUENIL have not been established in pediatric patients for the treatment of rheumatoid arthritis, chronic discoid lupus erythematosus, or systemic lupus erythematosus.

8.5 Geriatric Use

Clinical trials of PLAQUENIL did not include sufficient numbers of patients 65 years of age and older to determine whether they respond differently from younger adult patients. Nevertheless, this drug is known to be substantially excreted by the kidney, and the risk of toxic reactions to this drug may be greater in patients with impaired renal function. In general, dose selection in geriatric patients should start with the lowest recommended dose, taking into consideration the greater frequency of decreased hepatic, renal or cardiac function, and of concomitant disease or other drug therapy.

8.6 Patients with Renal or Hepatic Disease

A reduction in the dosage of PLAQUENIL may be necessary in patients with hepatic or renal disease.

10 OVERDOSAGE

PLAQUENIL overdosage symptoms have an onset within 1–3 hours of ingestion. The following have been reported with PLAQUENIL overdosage:
• Cardiovascular toxicity, including QRS or QTc prolongation, ventricular tachycardia, ventricular fibrillation, torsade de pointes, atrioventricular block, cardiac arrest and death.
• Life-threatening hypotension is common.
• Severe hypokalemia secondary to an intracellular shift is common in severe toxicity.
• Central nervous system (CNS) depression, seizures, visual disturbances, transient blindness, and coma may occur.
Gastrointestinal decontamination procedures warrant consideration in patients that present within the first hour post-ingestion. If the level of consciousness rapidly deteriorates in severe poisoning, consider intubation before gastrointestinal decontamination procedures. Monitor plasma potassium levels and manage accordingly. Hemofiltration, hemodialysis, and hemoperfusion are not of benefit.
Consider contacting a poison center (1-800-221-2222) or a medical toxicologist for overdosage management recommendations.

11 DESCRIPTION

PLAQUENIL (hydroxychloroquine sulfate) is an antimalarial and antirheumatic drug, chemically described as 2-[[4-[(7-Chloro-4- quinolyl) amino]pentyl] ethylamino]ethanol sulfate (1:1) with the molecular formula C18H26ClN3O•H2SO4. The molecular weight of hydroxychloroquine sulfate is 433.95. Its structural formula is:

Hydroxychloroquine sulfate is a white or off-white crystalline powder, freely soluble in water; practically soluble in alcohol, chloroform, and ether.
PLAQUENIL (hydroxychloroquine sulfate) tablets for oral administration contain 200 mg hydroxychloroquine sulfate (equivalent to 155 mg of hydroxychloroquine) and the following inactive ingredients: black iron oxide, carnauba wax, corn starch, dibasic calcium phosphate, hydroxypropyl methylcellulose, magnesium stearate, polyethylene glycol 400, polysorbate 80, titanium dioxide.

12 CLINICAL PHARMACOLOGY

12.1 Mechanism of Action

Malaria
Hydroxychloroquine is a 4-aminoquinoline antimalarial [see Microbiology (12.4)] and antirheumatic agent.
Rheumatoid Arthritis, Systemic Lupus Erythematosus and Chronic Discoid Lupus Erythematosus
The mechanisms underlying the anti-inflammatory and immunomodulatory effects of PLAQUENIL in the treatment of rheumatoid arthritis, chronic discoid lupus erythematosus and systemic lupus erythematosus are not fully known.

12.2 Pharmacodynamics

The exposure-response relationship and time course of pharmacodynamic response for the safety and effectiveness of hydroxychloroquine have not been fully characterized.

12.3 Pharmacokinetics

Following oral administration, the whole blood concentration of hydroxychloroquine at steady state is dose proportional over a dose range from 200 mg daily to 400 mg daily of PLAQUENIL in rheumatoid arthritis and lupus patients.

Absorption
Following a single 200 mg oral dose of PLAQUENIL to healthy male volunteers, whole blood hydroxychloroquine Cmax was 129.6 ng/mL (plasma Cmax was 50.3 ng/mL) with Tmax of 3.3 hours (plasma Tmax 3.7 hours). Peak blood concentrations of metabolites were observed at the same time as peak levels of hydroxychloroquine. Mean absolute oral bioavailability is 79% (SD: 12%) in fasting conditions.

Peak blood concentrations ranged from 1161 ng/mL to 2436 ng/mL (mean 1918 ng/mL) following a single dose of 155 mg intravenous infusion and from 2290 ng/mL to 4211 ng/mL (mean 3312 ng/mL) following a single dose of 310 mg intravenous infusion in healthy subjects. Pharmacokinetic parameters were not significantly different over the therapeutic dose range of 155 mg and 310 mg, indicating linear kinetics.

In patients with rheumatoid arthritis, there was large variability as to the fraction of the dose absorbed (i.e. 30 to 100%), and mean hydroxychloroquine levels were significantly higher in patients with less disease activity.

Distribution
PLAQUENIL is extensively distributed to tissues and has a large volume of distribution. Approximately 50% of hydroxychloroquine is bound to plasma proteins.

Metabolism
Significant levels of three metabolites, desethylhydroxychloroquine (DHCQ), desethylchloroquine (DCQ), and bidesethylhydroxychloroquine (BDCQ) were found in plasma and blood, with DHCQ being the major metabolite. In vitro, hydroxychloroquine is metabolized mainly by CYP2C8, CYP3A4 and CYP2D6 as well as by FMO-1 and MAO-A.

Elimination/Excretion
Renal clearance in patients with rheumatoid arthritis treated with PLAQUENIL for at least 6 months was similar to that in single dose studies in healthy volunteers, suggesting that no change in clearance occurred with chronic dosing. Renal clearance of unchanged hydroxychloroquine was approximately 16% to 30% of the dose after oral and IV administration. Results following a single oral dose of a 200 mg tablet demonstrated a half life of hydroxychloroquine about 40 days in whole blood. Following chronic oral administration of hydroxychloroquine, the absorption half-life of hydroxychloroquine was approximately 3 to 4 hours and the terminal half-life ranged from 40 to 50 days in whole blood. The effective half-life of hydroxychloroquine is likely to be shorter and steady state is achieved by 6 weeks following 400 mg daily oral administration in rheumatoid arthritis patients.

Drug Interaction Studies
In vitro study suggested that hydroxychloroquine has a potential to inhibit CYP2D6, CYP3A4, P-glycoproteins (P-gp), MATE1 and MATE2-K.

In vitro study suggested that hydroxychloroquine has no significant potential to inhibit CYP1A2, CYP2B6, CYP2C8, CYP2C9, CYP2C19, and the main transporters OATP1B1, OATP1B3, OAT1, OAT3, OCT1, and OCT2. In vitro, hydroxychloroquine has no significant potential to induce CYP1A2, CYP2B6 and CYP3A4.

12.4 Microbiology

Mechanism of Action in Malaria

The precise mechanism by which hydroxychloroquine exhibits activity against Plasmodium is not known. Hydroxychloroquine is a weak base and may exert its effect by concentrating in the acid vesicles of the parasite and inhibiting polymerization of heme. It can also inhibit certain enzymes by its interaction with DNA.
Antimicrobial Activity

Hydroxychloroquine is active against the erythrocytic forms of chloroquine sensitive strains of P. falciparum, P. malariae, P. vivax, and P. ovale. Hydroxychloroquine is not active against the gametocytes and exoerythrocytic forms including the hypnozoite liver stage forms of P. vivax and P. ovale.
Drug Resistance

P. falciparum strains exhibiting reduced susceptibility to chloroquine also show reduced susceptibility to hydroxychloroquine. Resistance of Plasmodium parasites to chloroquine is widespread [see Indications and Usage (1.1)].

13 NONCLINICAL TOXICOLOGY

13.1 Carcinogenesis, Mutagenesis, Impairment of Fertility

No carcinogenicity or genotoxicity studies have been conducted with hydroxychloroquine. No animal studies have been performed to evaluate the potential effects of hydroxychloroquine on reproduction or development, or to determine potential effects on fertility in males or females.

15 REFERENCES

^1 Center for Disease Control and Prevention. Malaria.
https://www.cdc.gov/parasites/malaria/index.html

16 HOW SUPPLIED/STORAGE AND HANDLING

16.1 How Supplied

PLAQUENIL tablets contain 200 mg hydroxychloroquine sulfate (equivalent to 155 mg base). White to off-white film coated, no score, tablet imprinted with “PLAQUENIL” on one face in black ink. The tablets are available in bottles of:
• 60 tablets - NDC 59212-562-60
• 100 tablets - NDC 59212-562-10 and NDC 59212-562-11

16.2 Storage

Dispense in a tight, light-resistant container as defined in the USP/NF.

Store at room temperature up to 30°C (86°F) and allow for excursions between 15°C and 30°C (59°F and 86°F).

17 PATIENT COUNSELING INFORMATION

Important Administration Instructions
Advise the patient to take PLAQUENIL with food or milk and not to crush or divide the tablet.
Cardiomyopathy and Ventricular Arrhythmias
Inform the patient that serious cardiac effects, life-threatening and fatal cases have been reported with use of PLAQUENIL. Advise patients to seek medical attention immediately if they experience any symptoms of heart rhythm changes including fast or irregular heartbeat, lightheadedness, dizziness, or syncope [see Warnings and Precautions (5.1)].
Retinal Toxicity
Inform the patient that irreversible retinal damage has been observed in some patients with the use of PLAQUENIL. Advise patients of the importance of the ophthalmology visits for monitoring their eyes. Instruct patients to seek medical attention promptly if they experience decreased vision or decreased dark adaptation [see Warnings and Precautions (5.2)].
Serious Skin Reactions
Inform the patient that severe, life-threatening skin reactions have been reported with the use of PLAQUENIL. Advise the patient to seek medical attention immediately if experiencing any of the following signs and symptoms: blisters on the skin, eyes, lips or in the mouth, itching or burning, with or without fever [see Warnings and Precautions (5.3)].
Hepatotoxicity Associated with Porphyria Cutanea Tarda
Inform the patient that liver toxicity has been reported in when PLAQUENIL was used in patients with porphyria cutanea tarda. In some cases, PCT was diagnosed only after the occurrence of liver injury, when PLAQUENIL was prescribed for an approved indication. Advise the patient to seek medical attention if experiencing fatigue, rash, nausea, dark urine, or jaundice [see Warnings and Precautions (5.5)].
Skeletal Muscle Myopathy or Neuropathy
Inform the patient that muscle weakness and atrophy has been reported with PLAQUENIL use. Advise patients to report to the physician symptoms of muscle weakness [see Warnings and Precautions (5.8)].
Neuropsychiatric Reactions Including Suicidality
Alert patients to seek medical attention immediately if they experience new or worsening depression, suicidal thoughts, or other mood changes [see Warnings and Precautions (5.9)].
Hypoglycemia
Inform the patient that PLAQUENIL has been associated with severe hypoglycemia. Advise the patient to monitor blood sugar levels if possible and to seek medical attention if experiencing any of the signs and symptoms of hypoglycemia such as sweating, shakiness, weakness, dizziness, tachycardia, nausea, blurred vision, confusion, fainting, or loss of consciousness [see Warnings and Precautions (5.10)].
Pregnancy
Inform the patient that there is a pregnancy registry that monitors pregnancy outcomes in women exposed to PLAQUENIL during pregnancy. Encourage patients to register by contacting 1-877-311-8972 [see Use in Specific Populations (8.1)].
Manufactured for:

Advanz Pharma (US) Corp.
Bannockburn, IL 60015

PLAQUENIL® is a registered trademark of Mercury Pharma Group Limited. Distributed by Advanz Pharma (US) Corp. under license.

PACKAGE LABEL.PRINCIPAL DISPLAY PANEL - 100 TABLET BOTTLE

NDC 59212-562-10 Rx only
Plaquenil®
hydroxychloroquine sulfate tablets, USP
200 mg 100 tablets
KEEP OUT OF THE REACH OF CHILDREN
Dispense in a tight, light-resistant container as defined in the USP/NF.
ADVANZ PHARMA

PACKAGE LABEL.PRINCIPAL DISPLAY PANEL - 60 TABLET BOTTLE

NDC 59212-562-60 Rx only
Plaquenil®
hydroxychloroquine sulfate tablets, USP
200 mg 60 tablets
KEEP OUT OF THE REACH OF CHILDREN
Dispense in a tight, light-resistant container as defined in the USP/NF.
ADVANZ PHARMA